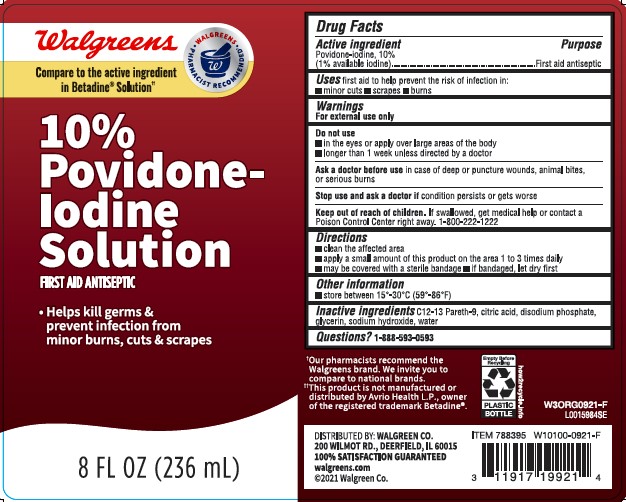 DRUG LABEL: First Aid Antiseptic
NDC: 0363-0777 | Form: SOLUTION
Manufacturer: Walgreen Co.
Category: otc | Type: HUMAN OTC DRUG LABEL
Date: 20260212

ACTIVE INGREDIENTS: POVIDONE-IODINE 10 mg/1 mL
INACTIVE INGREDIENTS: C12-13 PARETH-9; CITRIC ACID MONOHYDRATE; SODIUM PHOSPHATE, DIBASIC, ANHYDROUS; GLYCERIN; SODIUM HYDROXIDE; WATER

Walgreens 050.002/050AE
Povidone-Iodine Solution, 10%

Active ingredient

Povidone-iodine, 10% (1% available iodine)

Purpose

First aid antiseptic

Use

first aid to help prevent the risk of infection in:

- minor cuts
- scrapes
- burns

Warnings

For external use only

Do not use

- in the eyes or apply over large areas of the body
- longer than 1 week unless directed by a doctor

Ask a doctor before use

in case of deep or puncture wounds, animal bites, or serious burns

Stop use and ask a doctor if

condition persists or gets worse

Keep out of reach of children.

If swallowed, get medical help or contact a Poison Control Center right away.

Directions

- clean the affected area
- apply a small amount of this product on the area 1 to 3 times daily
- may be covered with a sterile bandage
- if bandaged, let dry first

Other information

- store between 15°-30° C (59°-86F)

inactive ingredients

C12-13 Pareth-9, citric acid, disodium phosphate, glycerin, sodium hydroxide, water

Questions?

1-888-593-0593

Claims

Our pharmacists recommend the Walgreens brand. We invite you to compare to national brands.

Disclaimer

‡This product or is not manufactured or distributed by Avrio Health L.P., owner of the registered trademark Betadine.

ADVERSE REACTION

DISTRIBUTED BY: WALGREEN CO.

200 WILMOT RD., DEERFIELD, IL 60015

100% SATISFACTION GUARANTEED

walgreens.com

©2021 Walgreen CO.

Empty Before Recycling

PLASTIC BOTTLE

how2recycle.info

principal display panel

Walgreens

WALGREENS PHARMACIST RECOMMENDED

Compare to the active ingredient in Betadine®Solution‡

10% Povidone-Iodine Solution

FIRST AID ANTISEPTIC

- Helps kill germs & prevent infection from minor burns, cuts & scrapes

8 FL OZ (236 mL)